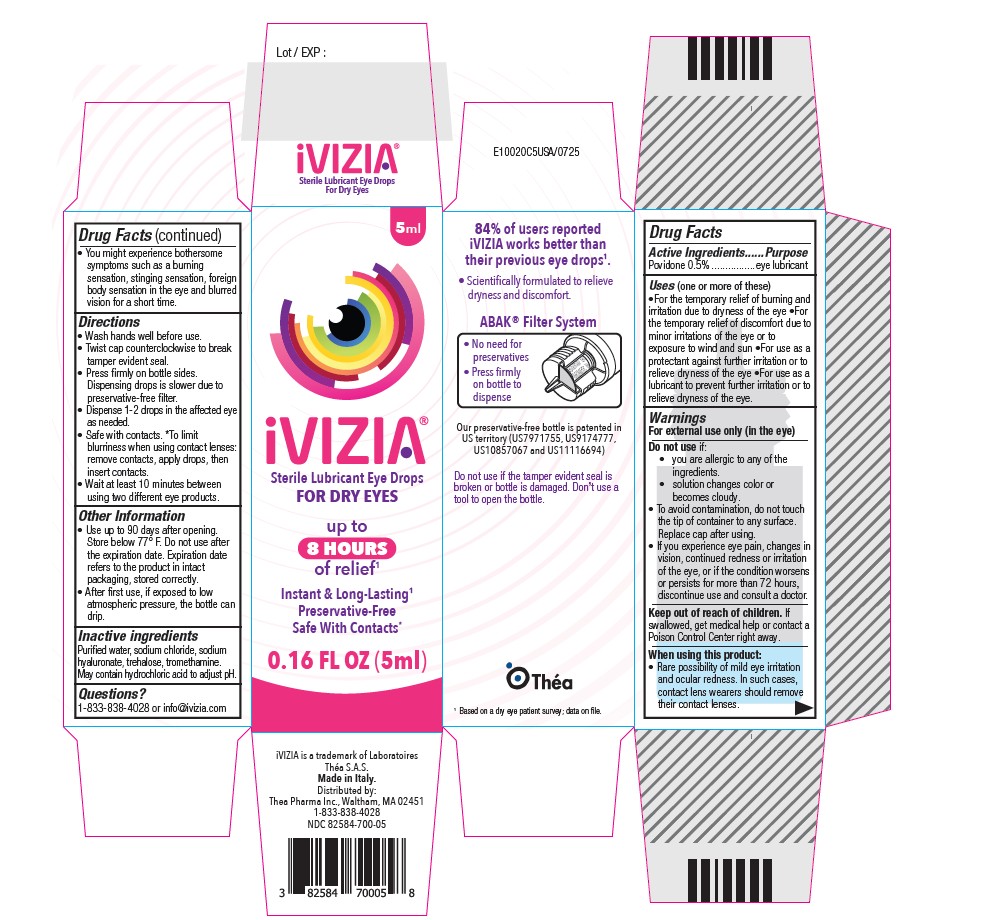 DRUG LABEL: iVIZIA Dry Eye
NDC: 82584-700 | Form: SOLUTION/ DROPS
Manufacturer: Thea Pharma Inc.
Category: otc | Type: HUMAN OTC DRUG LABEL
Date: 20251020

ACTIVE INGREDIENTS: POVIDONE 25 mg/5 mL
INACTIVE INGREDIENTS: WATER; HYALURONATE SODIUM; TREHALOSE; HYDROCHLORIC ACID; SODIUM CHLORIDE; TROMETHAMINE

iVIZIA Eye Drops

Active Ingredient

Povidone 0.5%

Purpose

Eye lubricant

Uses

(one or more of these)

For the temporary relief of burning and irritation due to dryness of the eye
For the temporary relief of discomfort due to minor irritations of the eye or to exposure to wind and sun
For use as a protectant against further irritation or to relieve dryness of the eye
For use as a lubricant to prevent further irritation or to relieve dryness of the eye.

Warnings

For external use only(in the eye)

Do not use if:
• you are allergic to any of the ingredients.
• solution changes color or becomes cloudy.
• To avoid contamination, do not touch the tip of container to any surface.
Replace cap after using.
• If you experience eye pain, changes in vision, continued redness or irritation of the eye, or if the condition worsens or persists for more than 72 hours, discontinue use and consult a doctor.

Keep out of reach of children.

If swallowed, get medical help or contact a Poison Control Center right away.

When using this product

Rare possibility of mild eye irritation and ocular redness. In such cases, contact lens wearers should remove their contact lenses.
You might experience bothersome symptoms such as a burning sensation, stinging sensation, foreign body sensation in the eye and blurred vision for a short time.

Directions:

Wash hands well before use.
Twist cap counterclockwise to break tamper evident seal.
Press firmly on bottle sides. Dispensing drops is slower due to preservative-free filter.
Dispense 1-2 drops in the affected eye as needed.
Safe with contacts. *To limit blurriness when using contact lenses: remove contacts, apply drops, then insert contacts.

Other Information

• Use up to 90 days after opening. Store below 77° F. Do not use after the expiration date on the carton. Expiration date refers to the product in intact packaging, stored correctly.
• After first use, if exposed to low atmospheric pressure, the bottle can drip.

Inactive Ingredients

Purified water, sodium chloride, sodium hyaluronate, trehalose, tromethamine. May contain hydrochloric acid to adjust pH.

Questions?

1-833-838-4028 or info@ivizia.com

Principle Display Panel

iVizia
Sterile Lubricant Eye Drops
For Dry Eyes
0.16 FL OZ (5ml)